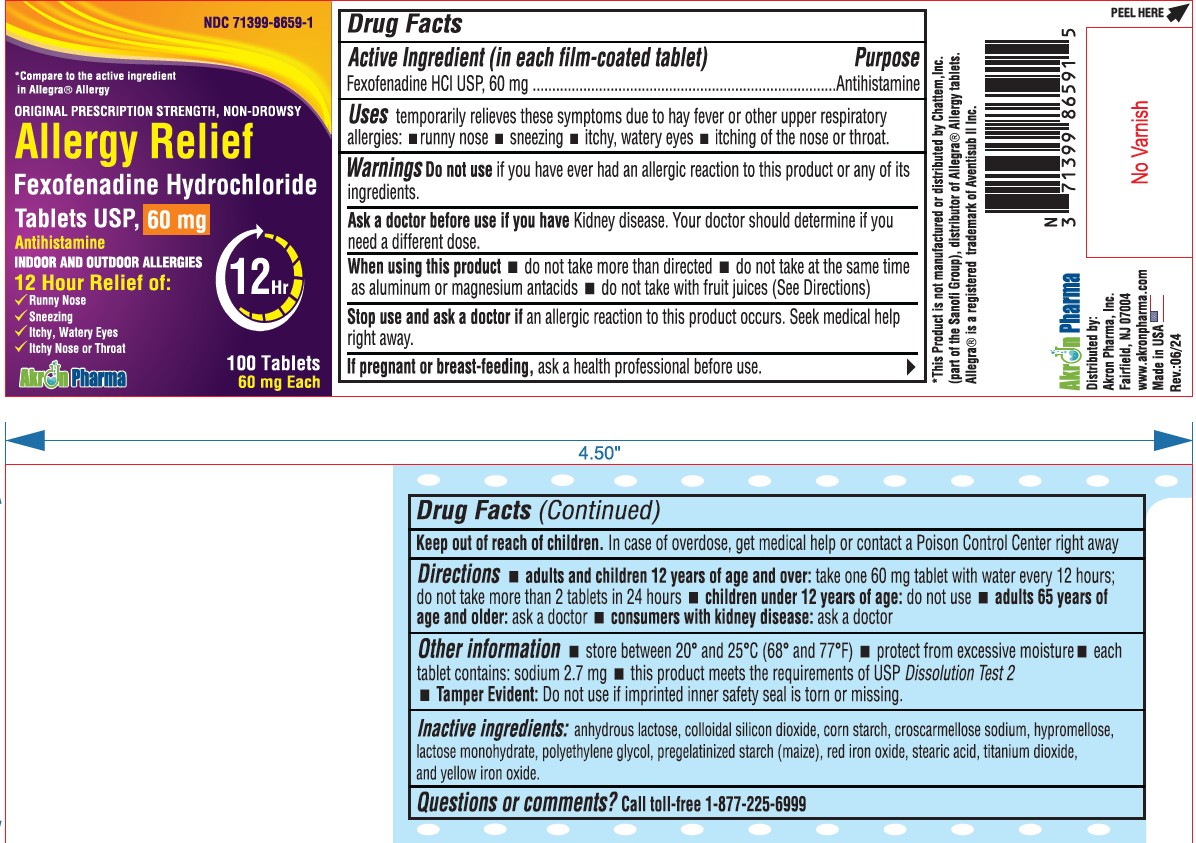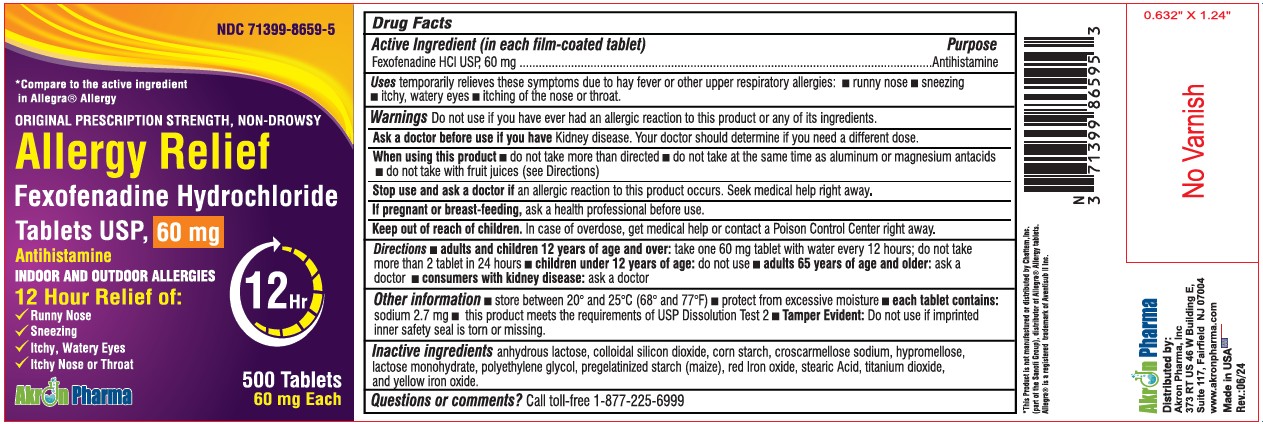 DRUG LABEL: fexofenadine hcl
NDC: 71399-8659 | Form: TABLET, FILM COATED
Manufacturer: AKRON PHARMA INC
Category: otc | Type: HUMAN OTC DRUG LABEL
Date: 20260119

ACTIVE INGREDIENTS: FEXOFENADINE HYDROCHLORIDE 60 mg/1 1
INACTIVE INGREDIENTS: ANHYDROUS LACTOSE; SILICON DIOXIDE; STARCH, CORN; CROSCARMELLOSE SODIUM; LACTOSE MONOHYDRATE; STEARIC ACID; HYPROMELLOSE, UNSPECIFIED; POLYETHYLENE GLYCOL, UNSPECIFIED; FERRIC OXIDE RED; TITANIUM DIOXIDE; FERRIC OXIDE YELLOW

ALLERGY Active ingredient (in each film-coated tablet)

Fexofenadine HCl USP 60 mg

Purpose

Antihistamine

Uses

temporarily relieves these symptoms due to hay fever or other upper respiratory allergies:

- runny nose
- sneezing
- itchy, watery eyes
- itching of the nose or throat

Warnings

Do not use

if you have ever had an allergic reaction to this product or any of its ingredients.

Ask a doctor before use if you have

kidney disease. Your doctor should determine if you need a different dose.

When using this product

- do not take more than directed
- do not take at the same time as aluminum or magnesium antacids
- do not take with fruit juices (see Directions)

Stop use and ask a doctor if

an allergic reaction to this product occurs. Seek medical help right away.

If pregnant or breast-feeding,

ask a health professional before use.

Keep out of reach of children.

In case of overdose, get medical help or contact a Poison Control Center right away.

Directions (for 60mg)

adults and children 12 years of age and over | take one 60mg tablet with water every 12 hours; do not take more than 2 tablets in 24 hours
children under 12 years of age | do not use
adults 65 years of age and older | ask a doctor
consumers with kidney disease | ask a doctor

Other information

- store between 20° and 25°C (68° and 77°F)
- protect from excessive moisture
- each tablet contains:sodium 2.7mg(for 60 mg)
- this product meets the requirements of USP Dissolution Test 2
- Tamper Evident:Do not use if imprinted inner safety seal is torn or missing

Inactive ingredients

anhydrous lactose, colloidal silicon dioxide, corn starch, croscarmellose sodium,hypromellose, lactose monohydrate, polyethylene glycol, pregelatinized starch(maize), red iron oxide, stearic acid, titanium dioxide and yellow iron oxide.

Questions or comments?

Call toll-free 1-877-225-6999

Distributed by:
Akron Pharma, Inc.
Fairfield, NJ 07004
www.akronpharma.com